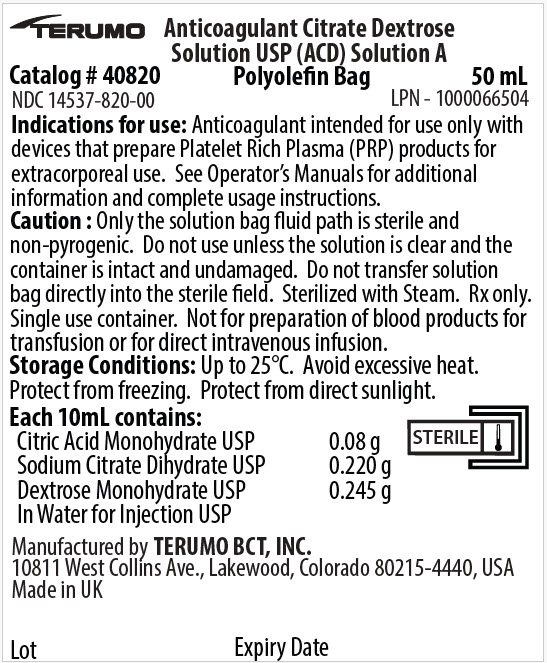 DRUG LABEL: Anticoagulant Citrate Dextrose (ACD-A)
NDC: 14537-820 | Form: SOLUTION
Manufacturer: Terumo BCT, Ltd
Category: prescription | Type: HUMAN PRESCRIPTION DRUG LABEL
Date: 20250121

ACTIVE INGREDIENTS: Dextrose Monohydrate 0.245 g/10 mL; Sodium Citrate, Unspecified Form 0.220 g/10 mL; Citric Acid Monohydrate 0.08 g/10 mL
INACTIVE INGREDIENTS: Water

HIGHLIGHTS OF PRESCRIBING INFORMATION

These highlights do not include all the information needed to use ANTICOAGULANT CITRATE DEXTROSE SOLUTION USP (ACD) SOLUTION A safely and effectively. See full prescribing information for ANTICOAGULANT CITRATE DEXTROSE SOLUTION USP (ACD) SOLUTION A.
ANTICOAGULANT CITRATE DEXTROSE SOLUTION USP (ACD) SOLUTION A
Sterile Fluid
Polyolefin Container (solution bag)
Clear Overwrap
Initial U.S. Approval: 2012

1 INDICATIONS AND USAGE

ANTICOAGULANT CITRATE DEXTROSE SOLUTION USP (ACD) SOLUTION A is an anticoagulant intended for use only with devices that prepare Platelet Rich Plasma (PRP) products for extracorporeal use. See the device operator's manual for additional information and complete usage instructions. (1)

2 DOSAGE AND ADMINISTRATION

- ANTICOAGULANT CITRATE DEXTROSE SOLUTION USP (ACD) SOLUTION A is added to blood products collected for extracorporeal processing. (2)
- ANTICOAGULANT CITRATE DEXTROSE SOLUTION USP (ACD) SOLUTION A may only be used with devices that prepare Platelet Rich Plasma (PRP) products for extracorporeal use. For instructions on the use of the solution see the device operator's manual. (2.1)
- Follow the directions for drawing ANTICOAGULANT CITRATE DEXTROSE SOLUTION USP (ACD) SOLUTION A into a syringe for further processing of the collected blood product. (2.2)

3 DOSAGE FORMS AND STRENGTHS

- 50 mL sterile fluid in a polyolefin solution bag. (3)

4 CONTRAINDICATIONS

- NOT FOR PREPARATION OF BLOOD PRODUCTS FOR TRANSFUSION OR FOR DIRECT INTRAVENOUS INFUSION. (4)

5 WARNINGS AND PRECAUTIONS

- Do not use the ANTICOAGULANT CITRATE DEXTROSE SOLUTION USP (ACD) SOLUTION A unless the solution is clear and the container is intact and undamaged. Use aseptic technique throughout all procedures to ensure donor safety and quality. (5)

6 ADVERSE REACTIONS

Citrate reactions or toxicity may occur with the injection of blood products containing citrate anticoagulant. The recipient of the blood product containing citrate should be monitored for the signs and symptoms of citrate toxicity. (6)

To report SUSPECTED ADVERSE REACTIONS, contact Terumo BCT, Inc. at 1-877-339-4228 or FDA at 1-800-FDA-1088 or www.fda.gov/medwatch.

8 USE IN SPECIFIC POPULATIONS

ANTICOAGULANT CITRATE DEXTROSE SOLUTION USP (ACD) SOLUTION A has not been studied in controlled clinical trials with specific populations.

FULL PRESCRIBING INFORMATION

1 INDICATIONS AND USAGE

ANTICOAGULANT CITRATE DEXTROSE SOLUTION USP (ACD) SOLUTION A is an anticoagulant intended for use only with devices that prepare Platelet Rich Plasma (PRP) products for extracorporeal use. [See Dosage and Administration (2).]

2 DOSAGE AND ADMINISTRATION

2.1 General Dosing Information

ANTICOAGULANT CITRATE DEXTROSE SOLUTION USP (ACD) SOLUTION A is added to blood products collected for extracorporeal processing. The solution is manually added to collected blood products to facilitate extracorporeal processing. The amount of solution added is specified by the manufacturer of the processing set. It is not intended for direct intravenous infusion.

For instructions on the use of the solution with the processing set, see the device operator's manual.

2.2 Administration

- Ensure solution is the ANTICOAGULANT CITRATE DEXTROSE SOLUTION USP (ACD) SOLUTION A and is within the expiration date.
- Inspect the solution bag. Do not use if the solution bag is damaged, leaking or if there is any visible sign of deterioration.
- Use only if solution is clear and free of particulate matter.
- Protect from sharp objects.

Directions for drawing the ANTICOAGULANT CITRATE DEXTROSE SOLUTION USP (ACD) SOLUTION A from the solution bag.

When directed by the processing set instructions and device operator's manual:

1. Open the foil pouch containing the solution by finding the notch in the foil overwrap and pulling down to present the clear overwrapped solution bag.
2. Open the clear overwrap material by holding the peelable tabs between your thumb and forefinger. Gently pull the peelable tabs along the top to open the overwrap at both corners. Once both corners are opened, gently peel along the length of the overwrap. Do not place the ANTICOAGULANT CITRATE DEXTROSE SOLUTION USP (ACD) SOLUTION A solution bag into the sterile field. The clear overwrap is not considered a sterile barrier.
3. Before use, perform the following checks [see Warnings and Precautions (5)]:
  - Check for leaks by gently squeezing the bag. If leaks are found, discard the solution bag.
  - Ensure that the solution is the ANTICOAGULANT CITRATE DEXTROSE SOLUTION USP (ACD) SOLUTION A and is within the expiration date.
  - Inspect the solution in adequate light. Solution showing cloudiness, haze, or particulate matter should not be used.
4. Aseptically prepare the Needleless Access Valve (NAV).
5. Using an appropriate syringe and luer, connect to the NAV.
6. Draw into the syringe the amount of ANTICOAGULANT CITRATE DEXTROSE SOLUTION USP (ACD) SOLUTION A required by the processing set instructions and device operator's manual.
7. Remove the syringe from the NAV and proceed according to the processing set instructions and device operator's manual.

Parenteral drug products should be inspected visually for particulate matter and discoloration prior to administration, whenever solution and solution bag permit.

3 DOSAGE FORMS AND STRENGTHS

50 mL ANTICOAGULANT CITRATE DEXTROSE SOLUTION USP (ACD) SOLUTION A is a sterile solution in a polyolefin solution bag. Each 100 mL contains: (%w/v) Citric Acid, Monohydrate 0.8 g; Dextrose Monohydrate 2.45 g; Sodium Citrate Dihydrate 2.2 g; and Water for Injection.

4 CONTRAINDICATIONS

NOT FOR PREPARATION OF BLOOD PRODUCTS FOR TRANSFUSION OR FOR DIRECT INTRAVENOUS INFUSION.

5 WARNINGS AND PRECAUTIONS

- Do not use the ANTICOAGULANT CITRATE DEXTROSE SOLUTION USP (ACD) SOLUTION A unless the solution is clear and the container is intact and undamaged.
- Do not transfer the solution bag directly into the sterile field.
- Do not reuse. Discard unused or partially used solution bags.
- Discard the product if the Needleless Access Valve (NAV) does not function as intended.
- Aseptically prepare the NAV before use.

6 ADVERSE REACTIONS

Citrate reactions or toxicity may occur with the injection of blood products containing citrate anticoagulant. The recipient of the blood product containing citrate should be monitored for the signs and symptoms of citrate toxicity. The signs and symptoms of citrate toxicity begin with paresthesia, a "tingling" sensation around the mouth or in the extremities, followed by severe reactions that are characterized by hypotension and possible cardiac arrhythmia. Citrate toxicity may occur more frequently in patients who are hypothermic, have impaired liver or renal function, or have low calcium levels because of an underlying disease.

8 USE IN SPECIFIC POPULATIONS

ANTICOAGULANT CITRATE DEXTROSE SOLUTION USP (ACD) SOLUTION A has not been studied in controlled clinical trials with specific populations.

11 DESCRIPTION

ANTICOAGULANT CITRATE DEXTROSE SOLUTION USP (ACD) SOLUTION A is designed to be added to blood products collected for extracorporeal processing, to prevent platelet activation and coagulation as blood moves throughout the extracorporeal processing set.

The content of the solution bag is considered sterile. This product has a sterile fluid path only. The clear overwrap is not considered a sterile barrier. The solution is non-pyrogenic, and it contains no bacteriostatic or antimicrobial agents.

The formulas of the active ingredients are provided in Table 1.

Table 1: Active Ingredients
Ingredients | Molecular Formula | Molecular Weight
(%w/v) Citric Acid, Monohydrate | C6H8O7 | 192.12
Dextrose Monohydrate | C6H12O6 ∙ H2O | 198.17
Sodium Citrate Dihydrate | C6H9Na3O9 | 294.10
Water for Injection | H2O | 18.00

Each 100 mL of ANTICOAGULANT CITRATE DEXTROSE SOLUTION USP (ACD) SOLUTION A contains: (%w/v) Citric Acid, Monohydrate 0.8 g; Dextrose Monohydrate 2.45 g; Sodium Citrate Dihydrate 2.2 g; and Water for Injection.

The solution bag is not made with natural rubber latex or PVC.

The solution bag is made from a polyolefin film. It contains materials that have been tested to demonstrate the suitability of the solution bag for storing pharmaceutical solutions. The solution contact layer is a polyolefin. The solution bag is nontoxic and biologically inert. The solution bag is a closed system and is not dependent upon entry of external air during administration. The solution bag is covered with a clear overwrap to provide protection from the physical environment. The content of the solution bag is considered sterile. This product has a sterile fluid path only. The clear overwrap is not considered a sterile barrier.

12 CLINICAL PHARMACOLOGY

12.1 Mechanism of Action

ANTICOAGULANT CITRATE DEXTROSE SOLUTION USP (ACD) SOLUTION A acts as an extracorporeal anticoagulant by binding the free calcium in the blood. Calcium is a necessary co-factor to several steps in the clotting cascade. The following ingredients are key components of the solution:

- Citric acid for pH regulation
- Sodium Citrate for anticoagulation
- Dextrose for isotonicity

This solution has no pharmacological effect.

16 HOW SUPPLIED/STORAGE AND HANDLING

ANTICOAGULANT CITRATE DEXTROSE SOLUTION USP (ACD) SOLUTION A is a clear sterile solution supplied in non-pyrogenic polyolefin solution bags. Each solution bag is individually wrapped in a clear overwrap. Each clear overwrap is then individually foil wrapped. Neither the clear overwrap nor the foil overwrap can be considered a sterile barrier. This product has a sterile fluid pathway only.

SIZE | CATALOG NUMBER | NDC NUMBER
50 mL | 40820 | Case: | 14537-820-03
 |  | Foil: | 14537-820-01
 |  | Bag: | 14537-820-00

STORAGE

Store up to 25 °C.

Avoid excessive heat. Protect from freezing. Protect from direct sunlight.

Issued: June 2024

Manufactured by
Terumo BCT, Inc.
Lakewood, CO 80215

Made in UK

PRINCIPAL DISPLAY PANEL - 50 mL Bag Pouch Case Label

TERUMO

Anticoagulant Citrate Dextrose
Solution USP (ACD) Solution A
Polyolefin Bag

Catalog # 40820
50 mL

NDC 14537-820-00
LPN - 1000066504

Indications for use: Anticoagulant intended for use only with
devices that prepare Platelet Rich Plasma (PRP) products for
extracorporeal use. See Operator's Manuals for additional
information and complete usage instructions.

Caution : Only the solution bag fluid path is sterile and
non-pyrogenic. Do not use unless the solution is clear and the
container is intact and undamaged. Do not transfer solution
bag directly into the sterile field. Sterilized with Steam. Rx only.
Single use container. Not for preparation of blood products for
transfusion or for direct intravenous infusion.

Storage Conditions: Up to 25°C. Avoid excessive heat.
Protect from freezing. Protect from direct sunlight.

Each 10mL contains:
Citric Acid Monohydrate USP
0.08 g
Sodium Citrate Dihydrate USP
0.220 g
Dextrose Monohydrate USP
0.245 g
In Water for Injection USP
STERILE

Manufactured by TERUMO BCT, INC.
10811 West Collins Ave., Lakewood, Colorado 80215-4440, USA
Made in UK

Lot
Expiry Date